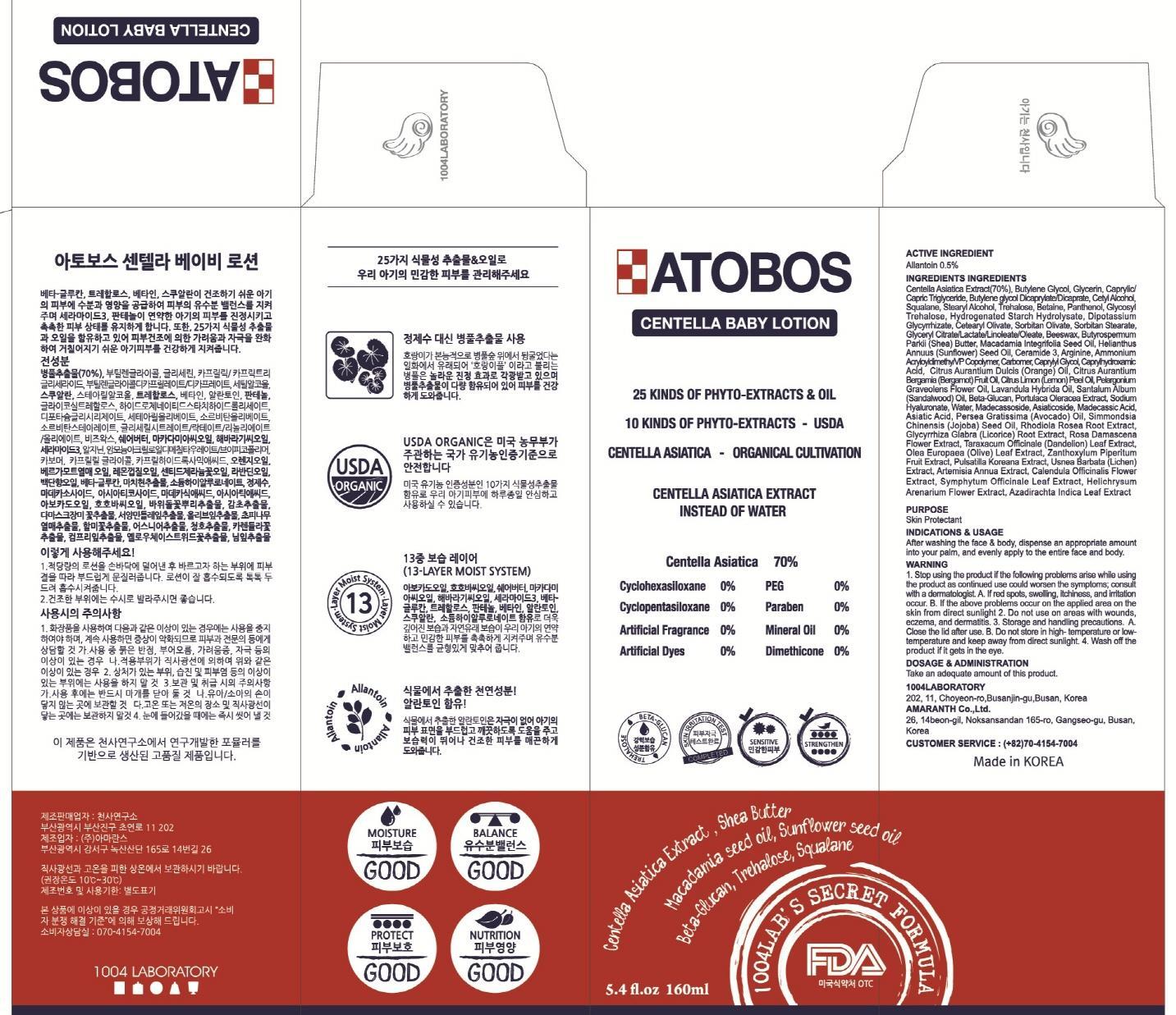 DRUG LABEL: ATOBOS CENTELLA BABY
NDC: 69739-080 | Form: LOTION
Manufacturer: 1004LABORATORY
Category: otc | Type: HUMAN OTC DRUG LABEL
Date: 20150831

ACTIVE INGREDIENTS: Allantoin 0.8 mg/160 mL
INACTIVE INGREDIENTS: CENTELLA ASIATICA; Butylene Glycol

ACTIVE INGREDIENT

Active Ingredient: Allantoin 0.5%

INACTIVE INGREDIENT

Inactive Ingredients: Centella Asiatica Extract(70%), Butylene Glycol, Glycerin, Caprylic/ Capric Triglyceride, Butylene glycol Dicaprylate/Dicaprate, Cetyl Alcohol, Squalane, Stearyl Alcohol, Trehalose, Betaine, Panthenol, Glycosyl Trehalose, Hydrogenated Starch Hydrolysate, Dipotassium Glycyrrhizate, Cetearyl Olivate, Sorbitan Olivate, Sorbitan Stearate, Glyceryl Citrate/Lactate/Linoleate/Oleate, Beeswax, Butyrospermum Parkii (Shea) Butter, Macadamia Integrifolia Seed Oil, Helianthus Annuus (Sunflower) Seed Oil, Ceramide 3, Arginine, Ammonium Acryloyldimethy/VP Copolymer, Carbomer, Caprylyl Glycol, Caprylhydroxamic Acid, Citrus Aurantium Dulcis (Orange) Oil, Citrus Aurantium Bergamia (Bergamot) Fruit Oil, Citrus Limon (Lemon) Peel Oil, Pelargonium Graveolens Flower Oil, Lavandula Hybrida Oil, Santalum Album (Sandalwood) Oil, Beta-Glucan, Portulaca Oleracea Extract, Sodium Hyaluronate, Water, Madecassoside, Asiaticoside, Madecassic Acid, Asiatic Acid, Persea Gratissima (Avocado) Oil, Simmondsia Chinensis (Jojoba) Seed Oil, Rhodiola Rosea Root Extract, Glycyrrhiza Glabra (Licorice) Root Extract, Rosa Damascena Flower Extract, Taraxacum Officinale (Dandelion) Leaf Extract, Olea Europaea (Olive) Leaf Extract, Zanthoxylum Piperitum Fruit Extract, Pulsatilla Koreana Extract, Usnea Barbata (Lichen) Extract, Artemisia Annua Extract, Calendula Officinalis Flower Extract, Symphytum Officinale Leaf Extract, Helichrysum Arenarium Flower Extract, Azadirachta Indica Leaf Extract

PURPOSE

Purpose: Skin Protectant

WARNINGS

Warnings: 1. Stop using the product if the following problems arise while using the product as continued use could worsen the symptoms; consult with a dermatologist. A. If red spots, swelling, itchiness, and irritation occur. B. If the above problems occur on the applied area on the skin from direct sunlight 2. Do not use on areas with wounds, eczema, and dermatitis. 3. Storage and handling precautions. A. Close the lid after use. B. Do not store in high- temperature or low- temperature and keep away from direct sunlight. 4. Wash off the product if it gets in the eye.

KEEP OUT OF REACH OF CHILDREN

INDICATIONS & USAGE

Indications & Usage: After washing the face & body, dispense an appropriate amount into your palm, and evenly apply to the entire face and body.

DOSAGE & ADMINISTRATION

Dosage & Administration: Take an adequate amount of this product.